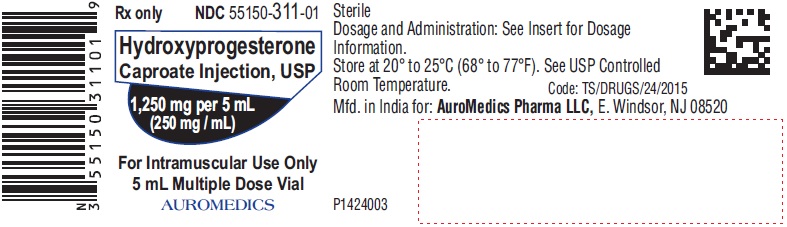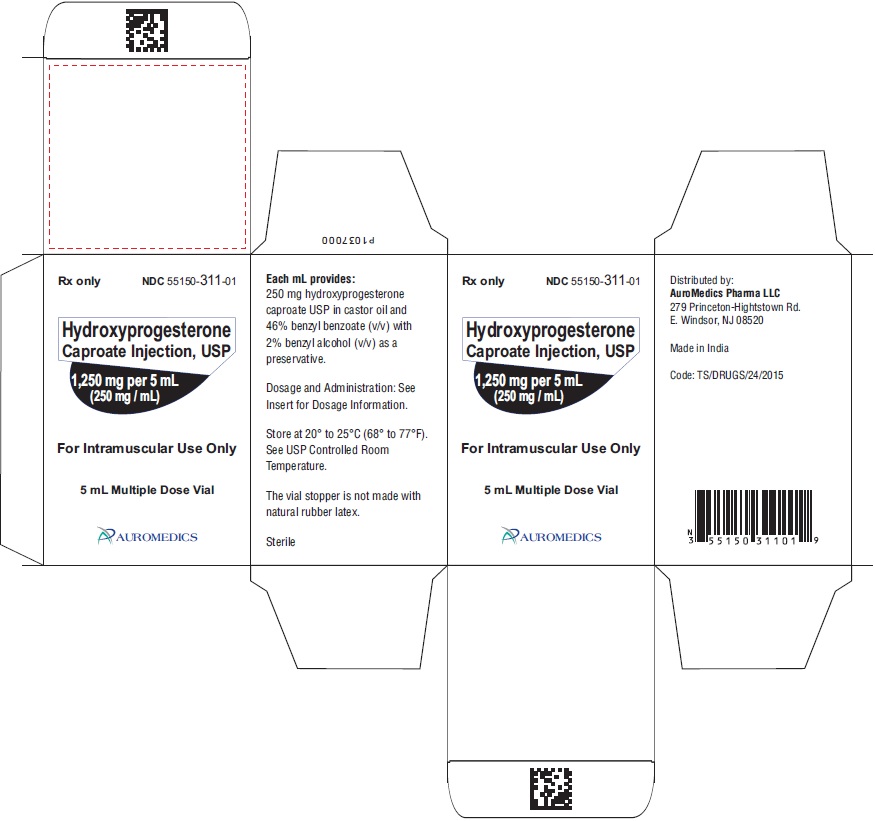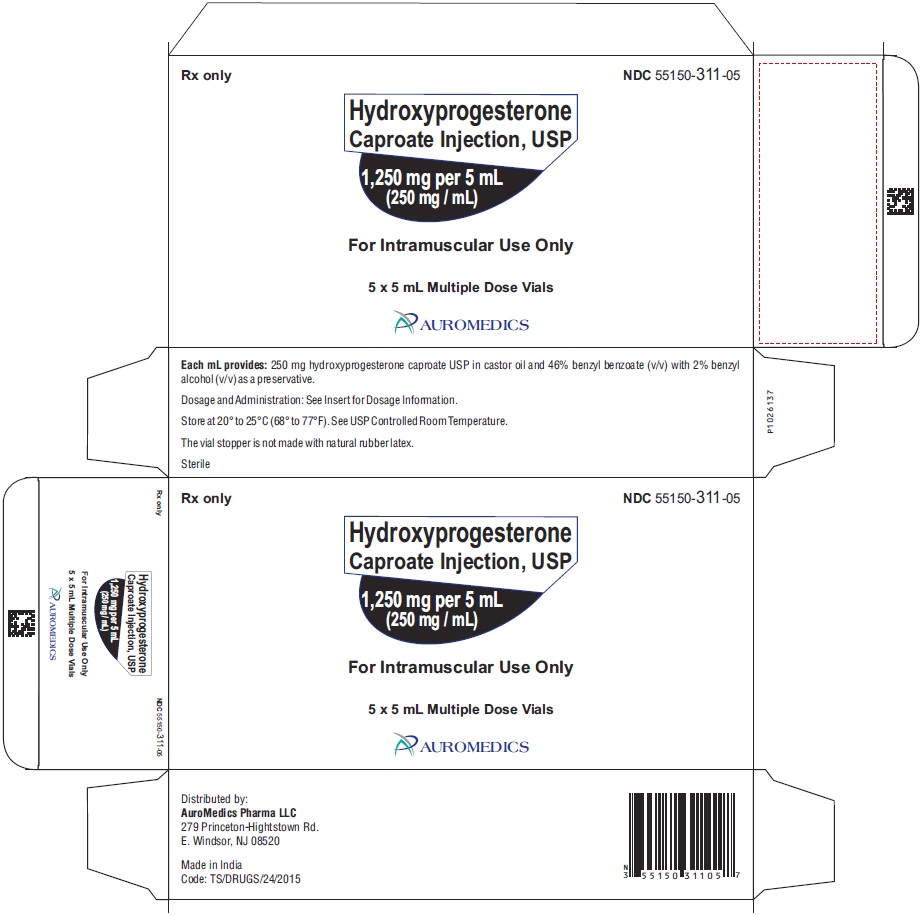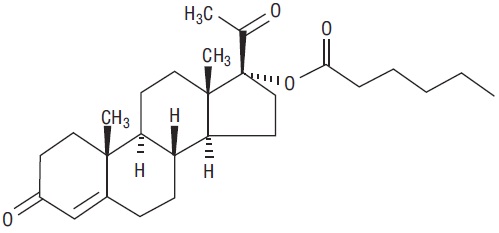 DRUG LABEL: Hydroxyprogesterone Caproate
NDC: 55150-311 | Form: INJECTION
Manufacturer: AuroMedics Pharma LLC
Category: prescription | Type: Human Prescription Drug Label
Date: 20220622

ACTIVE INGREDIENTS: HYDROXYPROGESTERONE CAPROATE 1250 mg/5 mL
INACTIVE INGREDIENTS: CASTOR OIL; BENZYL BENZOATE; BENZYL ALCOHOL

Hydroxyprogesterone Caproate Injection, USP
Rx only

DESCRIPTION

Hydroxyprogesterone Caproate Injection, USP is a sterile, long-acting preparation of the caproate ester of the naturally- occurring progestational hormone, hydroxyprogesterone, in an oil solution for intramuscular use.
The chemical name for hydroxyprogesterone caproate is pregn-4-ene-3,20-dione, 17[(1-oxohexyl)oxy]. It has a molecular formula of C27H40O4 and a molecular weight of 428.60. Hydroxyprogesterone caproate exists as white or creamy white crystalline powder.
The structural formula is:
Each 5 mL multiple-dose vial contains hydroxyprogesterone caproate, 250 mg/mL, in castor oil (28.6% v/v) and benzyl benzoate (46 % v/v) with the preservative benzyl alcohol (2% v/v).

CLINICAL PHARMACOLOGY

Hydroxyprogesterone is a potent, long-acting, progestational steroid ester which transforms proliferative endothelium into secretory endothelium, induces mammary gland duct development, and inhibits the production and/or release of gonadotropic hormone; it also shows slight estrogenic, androgenic, or corticoid effects as well, but should not be relied upon for these effects.
In advanced adenocarcinoma of the uterine corpus, Hydroxyprogesterone Caproate Injection, USP in a dosage of 1,000 mg or more, one or more times each week, often induces regressive changes.
Absorption: Peak serum levels of hydroxyprogesterone caproate appeared after 3 to 7 days in non-pregnant female subjects following a single intramuscular injection of 1,000 mg hydroxyprogesterone caproate. The pharmacokinetics of the 250 mg dose of hydroxyprogesterone caproate has not been evaluated in a study.
Metabolism: The conjugated metabolites include sulfated and glucuronidated products. In vitro data indicate that the metabolism of hydroxyprogesterone caproate is predominantly mediated by CYP3A4 and CYP3A5.
Excretion: Both conjugated metabolites and free steroids are excreted in the urine and feces, with the conjugated metabolites being prominent.
Hepatic Impairment
The effect of hepatic impairment on the pharmacokinetics of hydroxyprogesterone caproate has not been evaluated.
Hydroxyprogesterone caproate is extensively metabolized and hepatic impairment may reduce the elimination of hydroxyprogesterone caproate.
Renal Impairment
The effect of renal impairment on the pharmacokinetics of hydroxyprogesterone caproate has not been evaluated.

INDICATIONS AND USAGE

Hydroxyprogesterone Caproate Injection, USP is indicated in non-pregnant women: for the treatment of advanced adenocarcinoma of the uterine corpus (Stage III or IV); in the management of amenorrhea (primary and secondary) and abnormal uterine bleeding due to hormonal imbalance in the absence of organic pathology, such as submucous fibroids or uterine cancer; as a test for endogenous estrogen production and for the production of secretory endometrium and desquamation.

CONTRAINDICATIONS

Hydroxyprogesterone caproate is contraindicated in patients with known or suspected carcinoma of the breast, other hormone-sensitive cancer, or history of these conditions; undiagnosed abnormal vaginal bleeding; liver dysfunction or disease; missed abortion, and in those with a history of hypersensitivity to the drug. Hydroxyprogesterone caproate is also contraindicated as a diagnostic test for pregnancy and in patients with current or history of thrombotic or thromboembolic disorders.

WARNINGS

Thrombotic and Thromboembolic Events
Discontinue the medication pending examination if there is a sudden partial or complete loss of vision or if there is a sudden onset of proptosis, diplopia, or migraine. Medication should be stopped if examination reveals papilledema or retinal vascular lesions.
Allergic reactions
Hypersensitivity reaction to progestins have been reported. Hydroxyprogesterone caproate is contraindicated in women with a history of hypersensitivity to a progestin.
Glucose tolerance
Progestins may decrease glucose tolerance and the blood glucose concentration should be monitored in diabetic users.

PRECAUTIONS

Detectable amounts of progestins have been identified in the milk of mothers receiving the drug. Many studies have found no adverse effects of progestins on breastfeeding performance, or on the health, growth, or development of the infant.
Because progestational drugs may cause some degree of fluid retention, conditions that might be influenced by this effect, such as asthma, migraine, epilepsy, or cardiac or renal dysfunction require careful observation.
The pretreatment physical examination should include examination of the breasts and pelvic organs and a Papanicolaou smear.
In relation to irregular bleeding which does not respond predictably to the hormone therapy, nonfunctional causes should be borne in mind and adequate diagnostic measures instituted.
Any influence of prolonged sex hormone medication on pituitary, ovarian, adrenal, hepatic, or uterine function awaits further study.
The pathologist should be advised of progesterone therapy when relevant specimens are submitted.
Patients who have a history of psychic depression should be carefully observed and the drug discontinued if the depression recurs to a serious degree.

Information for The Patient

Counsel patients that hydroxyprogesterone caproate injections may cause pain, soreness, swelling, itching or bruising. Inform the patient to contact her physician if she notices increased discomfort over time, oozing of blood or fluid, or inflammatory reactions at the injection site.

ADVERSE REACTIONS

A. Serious arterial thrombotic and venous thromboembolic events, including cases of pulmonary emboli (some fatal), deep vein thrombosis, myocardial infarction, and strokes, have been reported in women using progestins.

B. neuroocular lesions (e.g., retinal thrombosis and optic neuritis); nausea; vomiting; gastrointestinal symptoms (such as abdominal cramps or bloating); edema; breakthrough bleeding, spotting, or withdrawal bleeding; breast tenderness; changes in body weight (increase or decrease); headache; increase in cervical mucus; allergic rash; abscess; pain at the injection site; migraine headaches.

C. chloasma or melasma, cholestatic jaundice, rise in blood pressure, mental depression, and amenorrhea during or after treatment.

D. posttreatment anovulation, cystitis, hirsutism, loss of scalp hair, changes in libido, changes in appetite, dizziness, fatigue, backache, itching, or amenorrhea.

E. The following laboratory tests may be affected by progestins: hepatic function (increased sulfobromophthalein retention and other tests); coagulation tests (increased in prothrombin and Factors VII, VIII, IX, and X); thyroid function tests (increase in PBI and butanol extractable protein-bound iodine, decrease in T3 uptake values.

A few instances of coughing, dyspnea, constriction of the chest, and/or allergic-like reactions have occurred following hydroxyprogesterone caproate therapy; the likelihood of these occurring may be increased at higher dosage levels.

DOSAGE AND ADMINISTRATION

Suggested dosages are presented in the therapy guide. Because of the low viscosity of the vehicle, Hydroxyprogesterone Caproate Injection, USP may be administered with a small gauge needle. Care should be taken to inject the preparation deeply into the upper outer quadrant of the gluteal muscle following the usual precautions for intramuscular injection. Since the 250 mg potency provides a high concentration in a small volume, particular care should be observed to administer the full dose.
Note: Use of a wet needle or syringe may cause the solution to become cloudy; however, this does not affect the potency of the material.
Parenteral drug products should be inspected visually for particulate matter and discoloration prior to administration, whenever solution and container permit.
Protect from light. Store vial in its box. Store upright.
Discard any unused product within 5 weeks after first use.

THERAPY GUIDE

CYCLIC THERAPY SCHEDULE: (28-day cycle; repeated every 4 weeks);
Day 1 of each cycle: 20 mg Estradiol Valerate Injection, USP
2 weeks after Day 1: 250 mg Hydroxyprogesterone Caproate Injection, USP and 5 mg Estradiol Valerate Injection, USP
4 weeks after Day 1. This is Day 1 of next cycle

SUGGESTED CYCLIC REGIMEN
Indications | Dosage | Started | Repeated | Stopped | Comments
Amenorrhea (primary and secondary): Abnormal uterine bleeding due to hormonal imbalance in the absence of organicpathology, such as submucous fibroids or uterine cancer. | 375 mg | Any time | - | - | Genital malignancy should be excluded before hormone therapy is started. Hydroxyprogesterone caproate is used as a “Medical D and C” to eliminate any proliferated endometrium from previous estrogenic action by conversion to secretory endometrium and desquamation. To determine onset of normal cyclic functions, patient should be observed for 2 or 3 cycles after cessation of therapy.
 | Cyclic Therapy Schedule | After 4 days of desquamation or, if there is no bleeding, 21 days after Hydroxyprogesterone Caproate Injection, USP alone | Every 4 weeks | After 4 cycles
Production of secretory endometrium and desquamation | Patients not on estrogen therapy: Cyclic Therapy Schedule | Any time | Every 4 weeks | When cyclic therapy is no longer required | If estrogen deficiency has been prolonged, menstruation may not occur until estrogen has been given for several months.
 | Patients currently on estrogen therapy: 375 mg Hydroxy progesterone Caproate Injection, USP | Any time | - | -
 | Cyclic Therapy Schedule | After 4 days of desquamation or, if there is no bleeding, 21 days after Hydroxyprogesterone Caproate Injection, USP alone | Every 4 weeks | When cyclic therapy is no longer required

SUGGESTED NON-CYCLIC REGIMEN
Indications | Dosage | Started | Repeated | Stopped | Comments
Adenocarcinoma of uterine corpus in advanced stage (Stage III or IV) | 1,000 mg or more | At once | 1 or more times each week (1 to 7 g per week) | When relapse occurs, or after 12 weeks with no objective response | Should not be used in early stage (Stage I or II) in place of established anticancer therapy. May be used in advanced stage concomitantly with other anticancer therapy (surgery, α radiation, or chemotherapy, or combination of these). Treatment results reported to date have been better in histologically well-differentiated forms of endometrial adenocarcinoma. (The drug has not been adequately studied in non-endometrioid adenocarcinoma of the uterine corpus).
Test for endogenous estrogen production ("Medical D and C") | 250 mg | Any time | For confirmation, 4 weeks after 1st injection | After 2nd injection | Non-pregnant patient with responsive endometrium; bleeding 7 to14 days after injection indicates endogenous estrogen.

HOW SUPPLIED

Hydroxyprogesterone Caproate Injection, USP is available in vials providing hydroxyprogesterone caproate with a potency of 250 mg per mL. The product is formulated in castor oil and 46% benzyl benzoate and containing 2% (v/v) benzyl alcohol as a preservative.
Hydroxyprogesterone Caproate Injection, USP is a sterile, clear pale yellow to yellow color oily solution and is supplied as follows:
5 mL Multiple-Dose Vial
Packaged Individually NDC 55150-311-01
5 mL Multiple-Dose Vials
in a carton of 5 NDC 55150-311-05
Storage
Hydroxyprogesterone Caproate Injection, USP should be stored at controlled room temperature 20° to 25° C (68° to 77° F). Storage at low temperatures may result in the separation of some crystalline material which redissolves readily on heating in boiling water.
Protect from light. Store vial in its box. Store upright.
Discard any unused product within 5 weeks after first use.
The vial stopper is not made with natural rubber latex.
Distributed by:
AuroMedics Pharma LLC
279 Princeton-Hightstown Road
E.Windsor, NJ 08520
Manufactured by:
Eugia Pharma Specialities Limited
Hyderabad – 500032
India
Revised: June 2022

PACKAGE LABEL-PRINCIPAL DISPLAY PANEL - 1,250 mg per 5 mL (250 mg / mL) - Container Label

Rx only NDC 55150-311-01
Hydroxyprogesterone
Caproate Injection, USP
1,250 mg per 5 mL
(250 mg / mL)
For Intramuscular Use Only
5 mL Multiple Dose Vial
AUROMEDICS

PACKAGE LABEL-PRINCIPAL DISPLAY PANEL - 1,250 mg per 5 mL (250 mg / mL) – Container-Carton (1 vial)

Rx only NDC 55150-311-01
Hydroxyprogesterone
Caproate Injection, USP
1,250 mg per 5 mL
(250 mg / mL)
For Intramuscular Use Only
5 mL Multiple Dose Vial
AUROMEDICS

PACKAGE LABEL-PRINCIPAL DISPLAY PANEL - 1,250 mg per 5 mL (250 mg / mL) – Container-Carton (5 vials)

Rx only NDC 55150-311-05
Hydroxyprogesterone
Caproate Injection, USP
1,250 mg per 5 mL
(250 mg / mL)
For Intramuscular Use Only
5 x 5 mL Multiple Dose Vials
AUROMEDICS